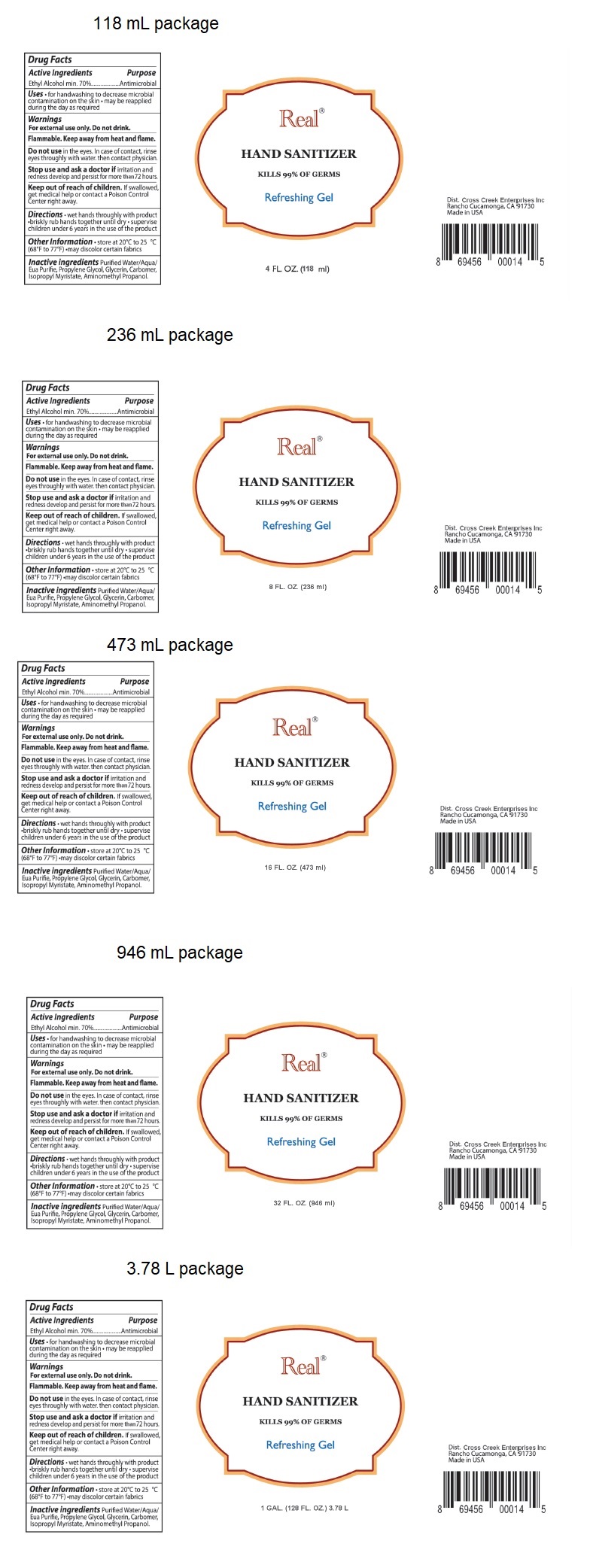 DRUG LABEL: Real HAND SANITIZER
NDC: 78568-920 | Form: GEL
Manufacturer: Cross Creek Enterprises Inc.
Category: otc | Type: HUMAN OTC DRUG LABEL
Date: 20200605

ACTIVE INGREDIENTS: ALCOHOL 70 mL/100 mL
INACTIVE INGREDIENTS: WATER; PROPYLENE GLYCOL; GLYCERIN; CARBOMER HOMOPOLYMER, UNSPECIFIED TYPE; ISOPROPYL MYRISTATE; AMINOMETHYLPROPANOL

Real® HAND SANITIZER

Active Ingredients

Ethyl Alcohol min. 70%

Purpose

Antimicrobial

INDICATIONS AND USAGE

Uses • for handwashing to decrease microbial contamination on the skin • may be reapplied during the day as required

Warnings

For external use only. Do not drink.

Flammable. Keep away from heat and flame.

Do not use in the eyes. In case of contact, rinse eyes thoroughly with water. then contact physician.

Stop use and ask a doctor if irritation and redness develop and persist for more than 72 hours.

Keep out of reach of children. If swallowed, get medical help or contact a Poison Control Center right away.

DOSAGE AND ADMINISTRATION

Directions • wet hands thoroughly with product • briskly rub hands together until dry • supervise children under 6 years in the use of the product

Other Information • store at 20°C to 25°C (68°F to 77°F) •may discolor certain fabrics

INACTIVE INGREDIENT

Inactive ingredients Purified Water/Aqua/Eua Purifie, Propylene Glycol, Glycerin, Carbomer, Isopropyl Myristate, Aminomethyl Propanol.

KILLS 99% OF GERMS

Refreshing Gel

Dist. Cross Creek Enterprises Inc

Rancho Cucamonga, CA 91730

Made in USA